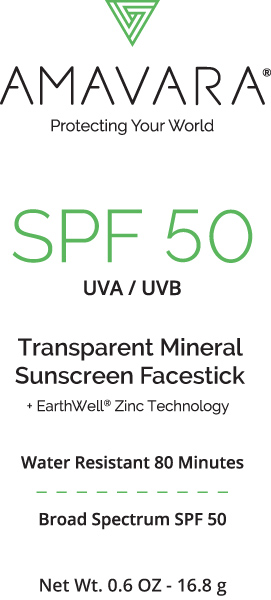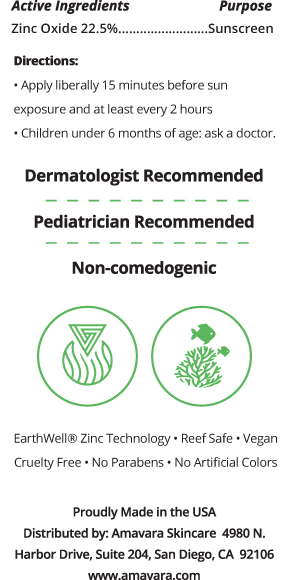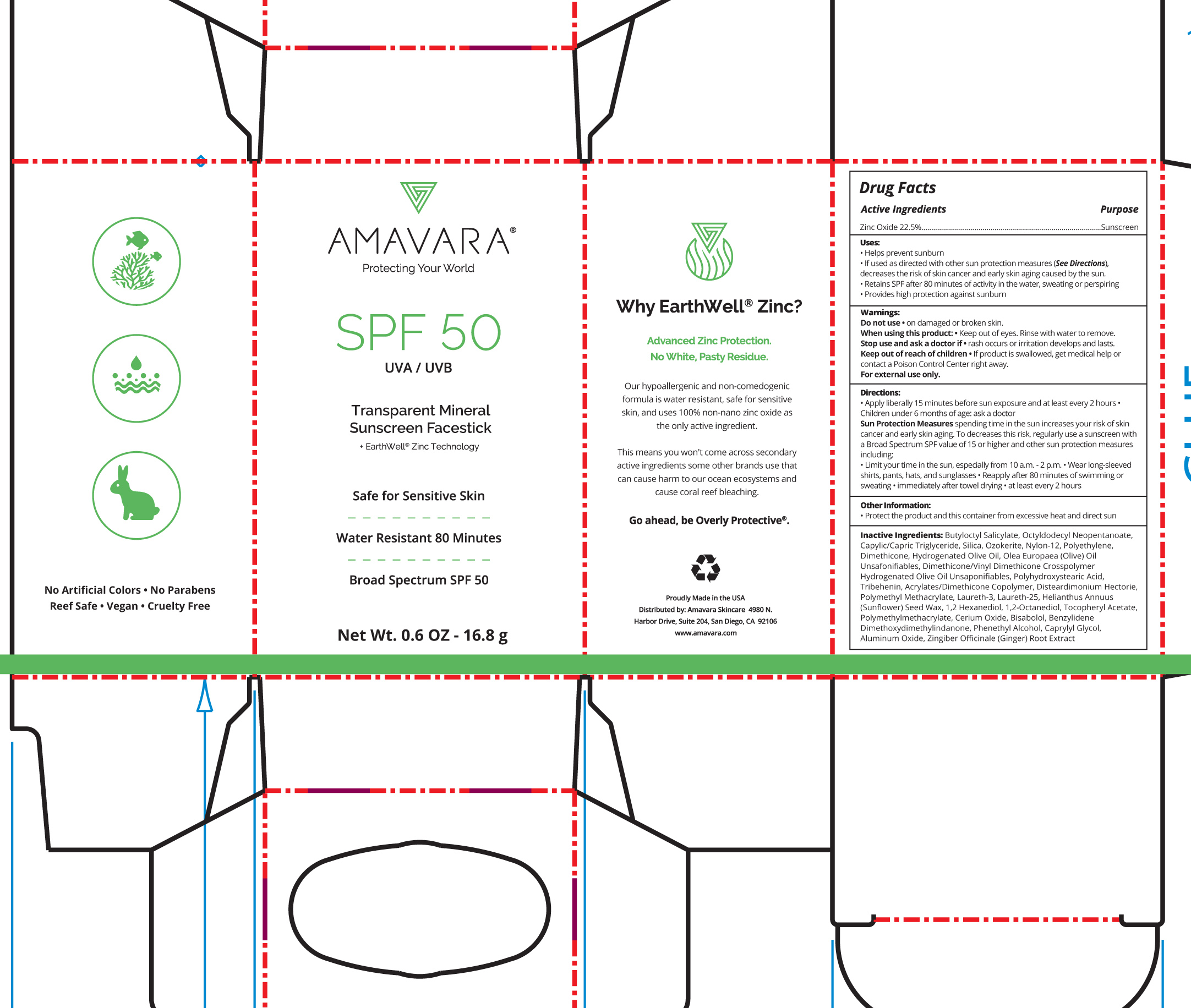 DRUG LABEL: Transparent Mineral Sunscreen Facestick Broad Spectrum SPF 50
NDC: 71942-103 | Form: STICK
Manufacturer: Amavara, Inc
Category: otc | Type: HUMAN OTC DRUG LABEL
Date: 20180508

ACTIVE INGREDIENTS: ZINC OXIDE 22.5 g/100 g
INACTIVE INGREDIENTS: DIMETHICONE/VINYL DIMETHICONE CROSSPOLYMER (SOFT PARTICLE); DISTEARDIMONIUM HECTORITE; CERIC OXIDE; LEVOMENOL; BENZYLIDENE DIMETHOXYDIMETHYLINDANONE; ALUMINUM OXIDE; TRIBEHENIN; LAURETH-3; BUTYLOCTYL SALICYLATE; CAPRYLYL GLYCOL; .ALPHA.-TOCOPHEROL ACETATE; OCTYLDODECYL NEOPENTANOATE; MEDIUM-CHAIN TRIGLYCERIDES; SILICON DIOXIDE; CERESIN; NYLON-12; LOW DENSITY POLYETHYLENE; DIMETHICONE; HYDROGENATED OLIVE OIL; POLYHYDROXYSTEARIC ACID (2300 MW); POLY(METHYL METHACRYLATE; 450000 MW); 1,2-HEXANEDIOL; PHENYLETHYL ALCOHOL; GINGER; OLEA EUROPAEA (OLIVE) OIL UNSAPONIFIABLES; HYDROGENATED OLIVE OIL UNSAPONIFIABLES; LAURETH-25; HELIANTHUS ANNUUS SEED WAX

Transparent Mineral Sunscreen Facestick SPF 50

Active Ingredients Purpose

Zinc Oxide 22.5% Sunscreen

Uses

- Helps Prevent Sunburn
- Higher SPF gives more sunburn protection
- If used as directed with other sun protection measures (see Directions), decreases the risk of skin cancer and early skin aging caused by the sun.
- Retains SPF after 80 minutes activity in the water, sweating, or perspiring.
- Provides high Protection against sunburn.

Keep out of reach of children

If product is swallowed, get medical help or contact a poison Control Center right away

Warnings

Do not use on damaged or broken skin

When using this product keep out of eyes. Rinse with water to remove

For external use only

Stop use and ask a doctor if

rash occurs or irritation develops and lasts.

Directions

• Apply liberally and generously 15 minutes before sun exposure and at least
every 2 hours. • Children under 6 months of age: ask a doctor.
• Sun Protection Measures Spending time in the sun increases your risk of
skin cancer and early skin aging. To decrease this risk, regularly use a
sunscreen with a Broad Spectrum SPF value of 15 or higher and other sun
protection measures including: • limit your time in the sun, especially from 10
a.m. – 2 p.m. • wear long-sleeved shirts, pants, hats, and sunglasses • Reapply:
• after 80 minutes of swimming or sweating • immediately after towel drying
• at least every 2 hours.

INACTIVE INGREDIENT

Inactive Ingredients: Butyloctyl Salicylate, Octyldodecyl Neopentanoate, Capylic/Capric Triglyceride, Silica, Ozokerite, Nylon-12, Polyethylene, Dimethicone, Hydrogenated Olive Oil, Olea Europaea (Olive) Oil Unsafonifiables, Dimethicone/Vinyl Dimethicone Crosspolymer Hydrogenated Olive Oil Unsaponifiables, Polyhydroxystearic Acid, Tribehenin, Acrylates/Dimethicone Copolymer, Disteardimonium Hectorie, Polymethyl Methacrylate, Laureth-3, Laureth-25, Helianthus Annuus (Sunflower) Seed Wax, 1,2 Hexanediol, 1,2-Octanediol, Tocopheryl Acetate, Polymethylmethacrylate, Cerium Oxide, Bisabolol, Benzylidene Dimethoxydimethylindanone, Phenethyl Alcohol, Caprylyl Glycol, Aluminum Oxide, Zingiber Officinale (Ginger) Root Extract

PACKAGE LABEL

Transparent Mineral Sunscreen Facestick

Safe for Sensitive Skin

Water Resistant 80 minutes

Broad Spectrum SPF 50

Net. Wt. 0.6 oz 16.8 g